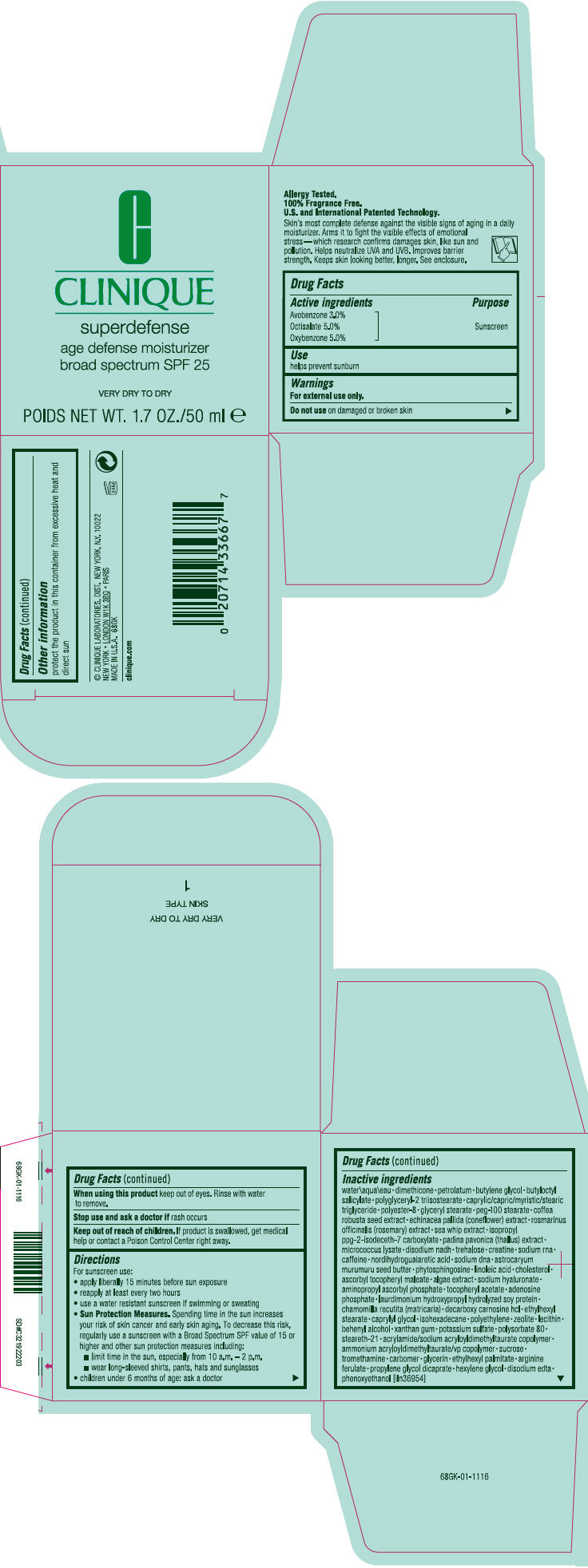 DRUG LABEL: SUPERDEFENSE AGE DEFENSE MOISTURIZER BROAD SPECTRUM SPF 25 VERY DRY TO DRY
NDC: 49527-034 | Form: CREAM
Manufacturer: CLINIQUE  LABORATORIES INC.
Category: otc | Type: HUMAN OTC DRUG LABEL
Date: 20130418

ACTIVE INGREDIENTS: OCTISALATE 0.0508 g/1 mL; OXYBENZONE 0.0508 g/1 mL; AVOBENZONE 0.0305 g/1 mL
INACTIVE INGREDIENTS: water; dimethicone; petrolatum; butylene glycol; butyloctyl salicylate; glyceryl monostearate; peg-100 stearate; robusta coffee bean; echinacea pallida; rosemary; pseudopterogorgia elisabethae; padina pavonica; trehalose; creatine; caffeine; masoprocol; astrocaryum murumuru seed butter; phytosphingosine; linoleic acid; cholesterol; ascorbyl tocopheryl maleate; hyaluronate sodium; aminopropyl ascorbyl phosphate; .alpha.-tocopherol acetate; adenosine phosphate; decarboxy carnosine Hydrochloride; ethylhexyl stearate; caprylyl glycol; isohexadecane; high density polyethylene; docosanol; xanthan gum; potassium sulfate; polysorbate 80; steareth-21; sucrose; ammonium acryloyldimethyltaurate/vp copolymer; tromethamine; glycerin; ethylhexyl palmitate; propylene glycol dicaprate; hexylene glycol; edetate disodium; phenoxyethanol

SUPERDEFENSE AGE DEFENSE MOISTURIZER BROAD SPECTRUM SPF 25 VERY DRY TO DRY

Drug Facts

Active ingredients

Avobenzone 3.0%
Octisalate 5.0%
Oxybenzone 5.0%

Purpose

Sunscreen

Use

helps prevent sunburn

Warnings

For external use only.

Do not use on damaged or broken skin

When using this product keep out of eyes. Rinse with water to remove.

Stop use and ask a doctor if rash occurs

Keep out of reach of children. If product is swallowed, get medical help or contact a Poison Control Center right away.

Directions

For sunscreen use:

- apply liberally 15 minutes before sun exposure
- reapply at least every two hours
- use a water resistant sunscreen if swimming or sweating
- Sun Protection Measures. Spending time in the sun increases your risk of skin cancer and early skin aging. To decrease this risk, regularly use a sunscreen with a Broad Spectrum SPF value of 15 or higher and other sun protection measures including:
  - limit time in the sun, especially from 10 a.m. – 2 p.m.
  - wear long-sleeved shirts, pants, hats and sunglasses
- children under 6 months of age: ask a doctor

Inactive ingredients

water\aqua\eau • dimethicone • petrolatum • butylene glycol • butyloctyl salicylate • polyglyceryl-2 triisostearate • caprylic/capric/myristic/stearic triglyceride • polyester-8 • glyceryl stearate • peg-100 stearate • coffea robusta seed extract • echinacea pallida (coneflower) extract • rosmarinus officinalis (rosemary) extract • sea whip extract • isopropyl ppg-2-isodeceth-7 carboxylate • padina pavonica (thallus) extract • micrococcus lysate • disodium nadh • trehalose • creatine • sodium rna • caffeine • nordihydroguaiaretic acid • sodium dna • astrocaryum murumuru seed butter • phytosphingosine • linoleic acid • cholesterol • ascorbyl tocopheryl maleate • algae extract • sodium hyaluronate • aminopropyl ascorbyl phosphate • tocopheryl acetate • adenosine phosphate • laurdimonium hydroxypropyl hydrolyzed soy protein • chamomilla recutita (matricaria) • decarboxy carnosine hcl • ethylhexyl stearate • caprylyl glycol • isohexadecane • polyethylene • zeolite • lecithin • behenyl alcohol • xanthan gum • potassium sulfate • polysorbate 80 • steareth-21 • acrylamide/sodium acryloyldimethyltaurate copolymer • ammonium acryloyldimethyltaurate/vp copolymer • sucrose • tromethamine • carbomer • glycerin • ethylhexyl palmitate • arginine ferulate • propylene glycol dicaprate • hexylene glycol • disodium edta • phenoxyethanol [iln36954]

Other information

protect the product in this container from excessive heat and direct sun

PRINCIPAL DISPLAY PANEL - 50 ml Jar Carton

C

CLINIQUE

superdefense

age defense moisturizer
broad spectrum SPF 25

VERY DRY TO DRY

POIDS NET WT. 1.7 OZ./50 ml e